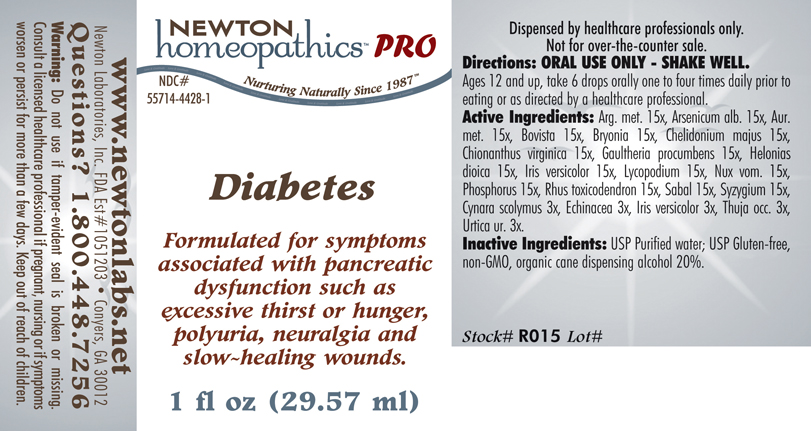 DRUG LABEL: Diabetes 
NDC: 55714-4428 | Form: LIQUID
Manufacturer: Newton Laboratories, Inc.
Category: homeopathic | Type: HUMAN PRESCRIPTION DRUG LABEL
Date: 20110601

ACTIVE INGREDIENTS: Silver 15 [hp_X]/1 mL; Arsenic Trioxide 15 [hp_X]/1 mL; Gold 15 [hp_X]/1 mL; Giant Puffball 15 [hp_X]/1 mL; Bryonia Alba Root 15 [hp_X]/1 mL; Chelidonium Majus 15 [hp_X]/1 mL; Chionanthus Virginicus Bark 15 [hp_X]/1 mL; Gaultheria Procumbens Top 15 [hp_X]/1 mL; Chamaelirium Luteum Root 15 [hp_X]/1 mL; Iris Versicolor Root 15 [hp_X]/1 mL; Lycopodium Clavatum Spore 15 [hp_X]/1 mL; Strychnos Nux-vomica Seed 15 [hp_X]/1 mL; Phosphorus 15 [hp_X]/1 mL; Toxicodendron Pubescens Leaf 15 [hp_X]/1 mL; Saw Palmetto 15 [hp_X]/1 mL; Syzygium Cumini Seed 15 [hp_X]/1 mL; Cynara Scolymus Leaf 3 [hp_X]/1 mL; Echinacea, Unspecified 3 [hp_X]/1 mL; Iris Versicolor Root 3 [hp_X]/1 mL; Thuja Occidentalis Leafy Twig 3 [hp_X]/1 mL; Urtica Urens 3 [hp_X]/1 mL
INACTIVE INGREDIENTS: Alcohol

Diabetes

PRODUCT NAME & INDICATIONS SECTION

Diabetes Formulated for symptoms associated with pancreatic dysfunction such as excessive thirst or hunger, polyuria, neuralgia and slow-healing wounds.

DIRECTION SECTION

Directions: ORAL USE ONLY - SHAKE WELL. Ages 12 and up, take 6 drops orally one to four times daily prior to eating or as directed by a healthcare professional.

ACTIVE INGREDIENT SECTION

Arg. met. 15x, Arsenicum alb 15x, Aur. met. 15x, Bovista 15x, Bryonia 15x, Chelidonium majus 15x, Chionanthus virginica 15x, Gaultheria procumbens 15x, Helonias dioica 15x, Iris versicolor 15x, Lycopodium 15x, Nux vom 15x, Phosphorus 15x, Rhus toxicodendron 15x, Sabal 15x, Syzygium 15x, Cynara 3x, Echinacea 3x, Iris versicolor 3x, Thuja occ. 3x, Urtica ur. 3x.

PURPOSE SECTION

Formulated for symptoms associated with pancreatic dysfunction such as excessive thirst or hunger, polyuria, neuralgia and slow-healing wounds.

INACTIVE INGREDIENT SECTION

Inactive Ingredients: USP Purified Water; USP Gluten-free, non-GMO, organic cane dispensing alcohol 20%.

QUESTIONS? SECTION

www.newtonlabs.net Newton Laboratories, Inc. FDA Est # 1051203 - Conyers, GA 30012
Questions? 1.800.448.7256

WARNINGS SECTION

Warning: Do not use if tamper - evident seal is broken or missing. Consult a licensed healthcare professional if pregnant, nursing or if symptoms worsen or persist for more than a few days. Keep out of reach of children.

OTC - PREGNANCY OR BREAST FEEDING SECTION

Consult a licensed healthcare professional if pregnant or nursing or if symptoms worsen or persist for more than a few days.

OTC - KEEP OUT OF REACH OF CHILDREN SECTION

Keep out of reach of children.